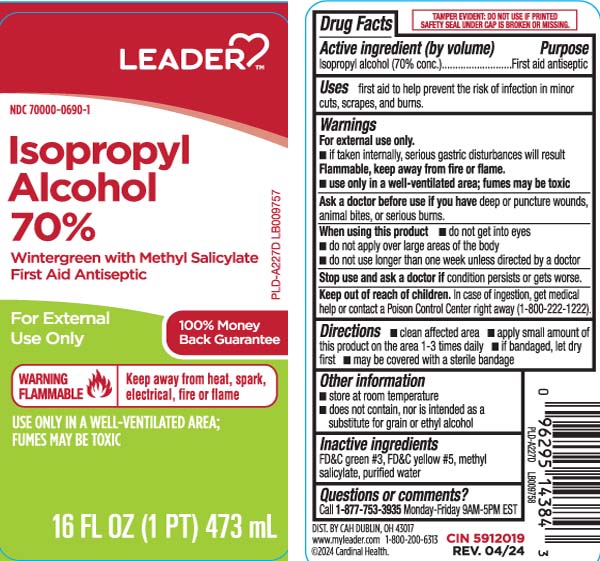 DRUG LABEL: Isopropyl Alcohol
NDC: 70000-0690 | Form: LIQUID
Manufacturer: Cardinal Health (Leader) 70000
Category: otc | Type: HUMAN OTC DRUG LABEL
Date: 20250711

ACTIVE INGREDIENTS: ISOPROPYL ALCOHOL 70 mL/100 mL
INACTIVE INGREDIENTS: FD&C GREEN NO. 3; FD&C YELLOW NO. 5; METHYL SALICYLATE; WATER

Drug Facts

Active ingredient (by volume)

Isopropyl alcohol (70% conc.)

Purpose

First aid antiseptic

Uses

first aid to help prevent the risk of infection in minor cuts, scrapes and burns

Warnings

For external use only.

- if taken internally, serious gastric disturbances will result

flammable, keep away from fire or flame

- use only in a well-ventilated area; fumes may be toxic

Ask a doctor before use if you have

deep or puncture woods, animal bites or serious burns

When using this product

- do not get into eyes
- do not apply over large areas of the body
- do not use longer than one week unless directed by a doctor

Stop use and ask a doctor if

condition persists or gets worse

Keep out of reach of children.

In case of ingestion, get medical help or contact a Poison Control Center right away (1-800-222-1222).

Directions

- clean affected area
- apply small amount of this product on the area 1-3 times daily
- if bandaged, let dry first
- may be covered with a sterile bandage

Other information

- store at room temperature
- does not contain, nor is intended as a substitute for grain or ethyl alcohol

Inactive ingredients

FD&C green #3, FD&C yellow #5, methyl salicylate, purified water

Principal Display Panel

Isopropyl Alcohol 70%

Wintergreen with Methyl Salicylate

First Aid Antiseptic

For External Use Only

WARNING: FLAMMABLE | keep away from heat, spark, electrical, fire or flame

USE ONLY IN A WELL-VENTILATED AREA;

FUMES MAY BE TOXIC

FL OZ (mL)

TAMPER EVIDENT: DO NOT USE IF PRINTED SAFETY SEAL UNDER THE CAP IS BROKEN OR MISSING.

DIST. BY CAH DUBLIN, OH 43017

Package Label

LEADER Isopropyl Alcohol 70% Wintergreen